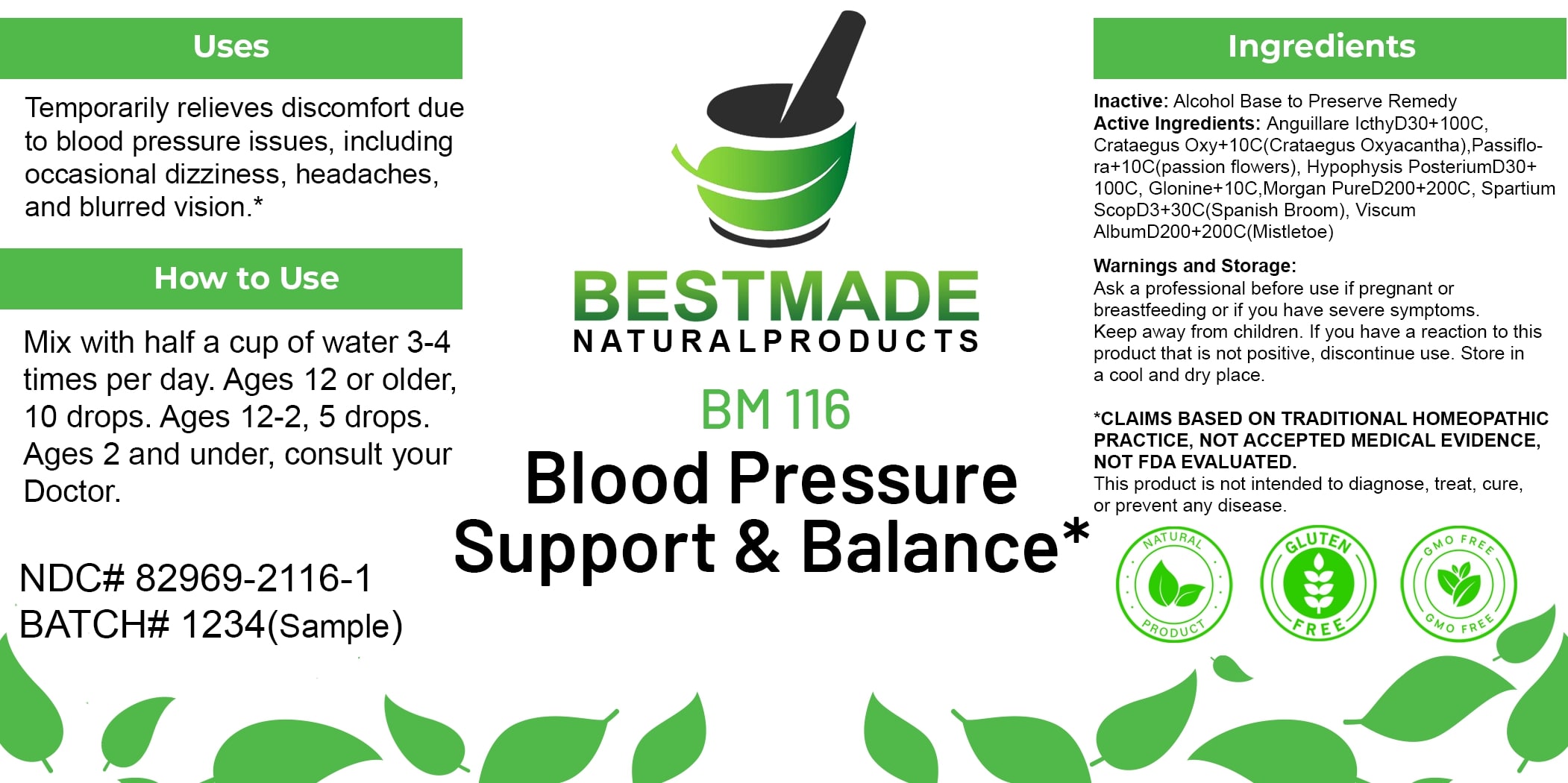 DRUG LABEL: Bestmade Natural Products BM116
NDC: 82969-2116 | Form: LIQUID
Manufacturer: Bestmade Natural Products
Category: homeopathic | Type: HUMAN OTC DRUG LABEL
Date: 20250207

ACTIVE INGREDIENTS: NITROGLYCERIN 30 [hp_C]/30 [hp_C]; PASSIFLORA INCARNATA FLOWERING TOP 30 [hp_C]/30 [hp_C]; PROTEUS MORGANII 30 [hp_C]/30 [hp_C]; VISCUM ALBUM FRUITING TOP 30 [hp_C]/30 [hp_C]; CYTISUS SCOPARIUS FLOWERING TOP 30 [hp_C]/30 [hp_C]; CRATAEGUS LAEVIGATA WHOLE 30 [hp_C]/30 [hp_C]; SUS SCROFA PITUITARY GLAND, POSTERIOR 30 [hp_C]/30 [hp_C]; ANGUILLA ROSTRATA BLOOD SERUM 30 [hp_C]/30 [hp_C]
INACTIVE INGREDIENTS: ALCOHOL 30 [hp_C]/30 [hp_C]

BM116

DOSAGE AND ADMINISTRATION

How to Use

Mix with half a cup of water 3-4 times per day. Ages 12 or older, 10 drops. Ages 12-2, 5 drops. Ages 2 and under, consult your Doctor.

INACTIVE INGREDIENT

Ingredients

Inactive: Alcohol Base to Preserve Remedy

ACTIVE INGREDIENT

Active Ingredients: Anguillare IcthyD30+100C, Crataegus Oxy+10C(Crataegus Oxyacantha), Passiflora+10C(passion flowers), Hypophysis PosteriumD30+100C, Glonine+10C, Morgan PureD200+200C, Spartium ScopD3+30C(Spanish Broom), Viscum AlbumD200+200C(Mistletoe)

Uses

Temporarily relieves discomfort due to blood pressure issues, including occasional dizziness, headaches, and blurred vision.*

*CLAIMS BASED ON TRADITIONAL HOMEOPATHIC PRACTICE, NOT ACCEPTED MEDICAL EVIDENCE, NOT FDA EVALUATED.

This product is not intended to diagnose, treat, cure, or prevent any disease.

Uses

Temporarily relieves discomfort due to blood pressure issues, including occasional dizziness, headaches, and blurred vision.*

*CLAIMS BASED ON TRADITIONAL HOMEOPATHIC PRACTICE, NOT ACCEPTED MEDICAL EVIDENCE, NOT FDA EVALUATED.

This product is not intended to diagnose, treat, cure, or prevent any disease.

KEEP OUT OF REACH OF CHILDREN

Warnings and Storage:

Ask a professional before use if pregnant or breastfeeding or if you have severe symptoms. Keep away from children. If you have a reaction to this product that is not positive, discontinue use. Store in a cool and dry place.

Warnings and Storage:

Ask a professional before use if pregnant or breastfeeding or if you have severe symptoms. Keep away from children. If you have a reaction to this product that is not positive, discontinue use. Store in a cool and dry place.

*CLAIMS BASED ON TRADITIONAL HOMEOPATHIC PRACTICE, NOT ACCEPTED MEDICAL EVIDENCE, NOT FDA EVALUATED. This product is not intended to diagnose, treat, cure, or prevent any disease.

Entire package label